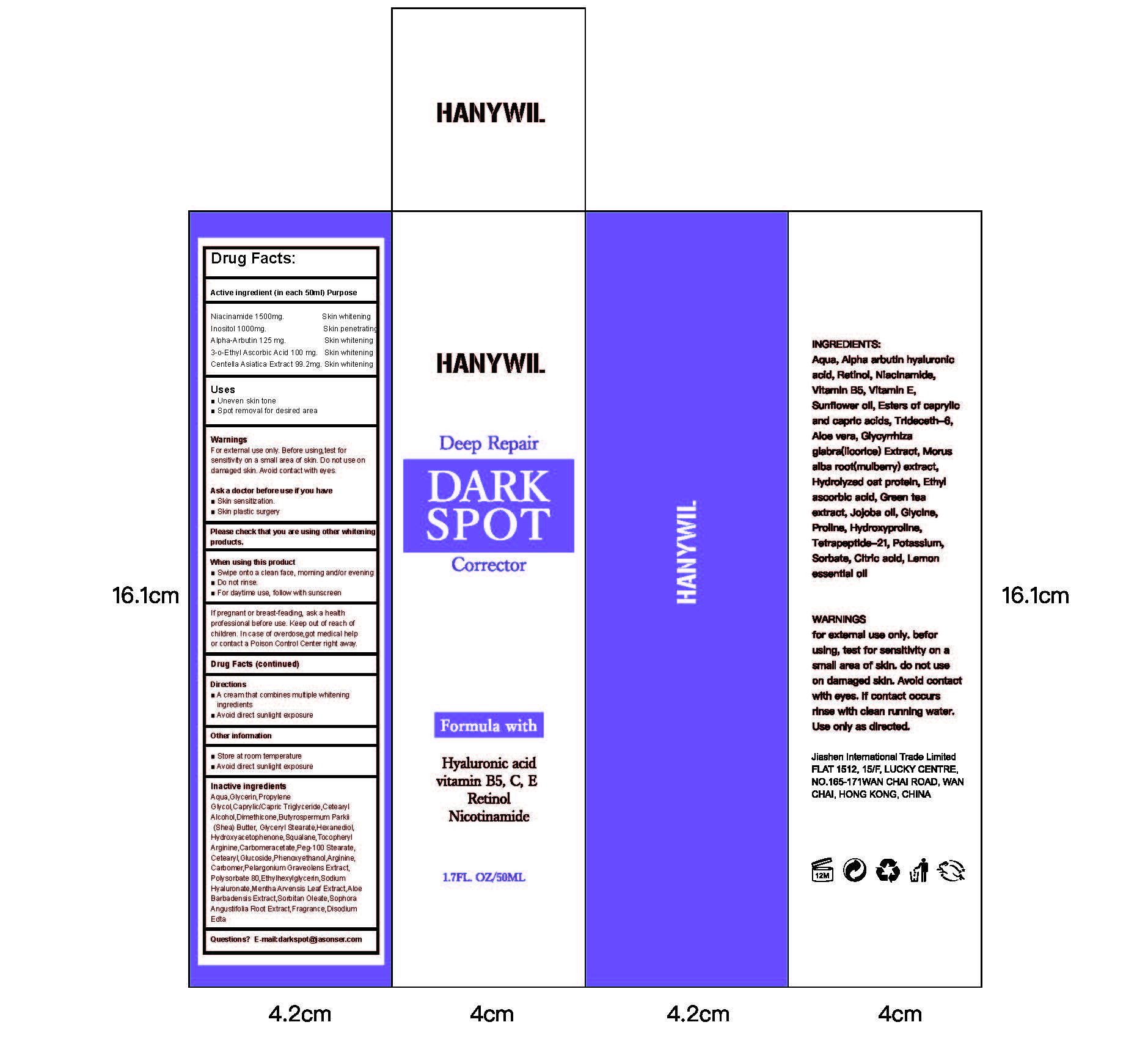 DRUG LABEL: HANYWIL Deep Repair DARK SPOT
NDC: 84867-002 | Form: CREAM
Manufacturer: Jiashen International Trading Co., Ltd.
Category: otc | Type: HUMAN OTC DRUG LABEL
Date: 20241105

ACTIVE INGREDIENTS: CENTELLA ASIATICA TRITERPENOIDS 99.2 mg/50 mL; INOSITOL 1000 mg/50 mL; ALPHA-ARBUTIN 125 mg/50 mL; NIACINAMIDE 1500 mg/50 mL; 3-O-ETHYL ASCORBIC ACID 100 mg/50 mL
INACTIVE INGREDIENTS: CAPRYLIC/CAPRIC TRIGLYCERIDE; SOPHORA FLAVESCENS ROOT; MENTHA ARVENSIS LEAF; ALOE BARBADENSIS LEAF EXTRACT; PHENOXYETHANOL; EDETATE DISODIUM; ALPHA-TOCOPHEROL ACETATE; ETHYLHEXYLGLYCERIN; CHRYSANTHELLUM INDICUM TOP; PELARGONIUM GRAVEOLENS LEAF OIL; 1,2-HEXANEDIOL; DIMETHICONE 350; BUTYROSPERMUM PARKII (SHEA) BUTTER; FRAGRANCE 13576; GLYCERYL STEARATE/PEG-100 STEARATE; CETEARYL ALCOHOL; GLYCERIN; CARBOMER; SQUALANE; PROPYLENE GLYCOL; PURSLANE; CETEARYL GLUCOSIDE; HYDROXYACETOPHENONE; HAMAMELIS VIRGINIANA TOP WATER

ACTIVE INGREDIENT

Niacinamide 1500mg.Inositol 1000mg.Alpha-Arbutin 125 mg.3-0-Ethyl Ascorbic Acid 100 mg.Centella Asiatica Extract 99.2mg

INACTIVE INGREDIENT

WATER
GLYCERIN
PROPYLENE GLYCOL
CAPRYLIC/CAPRIC TRIGLYCERIDE
CETEARYL ALCOHOL
CETEARYL GLUCOSIDE
DIMETHICONE 350
BUTYROSPERMUM PARKII (SHEA) BUTTER
GLYCERYL STEARATE
PURSLANE
CHRYSANTHELLUM INDICUM TOP
PELARGONIUM GRAVEOLENS OIL
MENTHA ARVENSIS LEAF EXTRACT
ALOE BARBADENSIS EXTRACT
SOPHORA ANGUSTIFOLIA ROOT EXTRACT
SQUALANE
TOCOPHERYL ACETATE
1,2-HEXANEDIOL
HYDROXYACETOPHENONE
PHENOXYETHANOL
ETHYLHEXYLGLYCERIN
CARBOMER
DISODIUM EDTA
FRAGRANCE

PURPOSE

Deep Repair
DARKSPOT
Corrector

WARNINGS

WarningsFor extemnal use only. Before using,test forsensitivity on a small area of skin. Do not use ondamaged skin. Avoid contact with eyes.
Ask a doctor before use if you have
Skin sensitization.
Skin plastic surgery

STOP USE

If pregnant or breast-feading, ask a healthprofessional before use. Keep out of reach ofchildren.in case of overdose,got medical helpor contact a Poison Control Center right away.

DO NOT USE

If pregnant or breast-feading, ask a healthprofessional before use. Keep out of reach ofchildren.in case of overdose,got medical helpor contact a Poison Control Center right away.

KEEP OUT OF REACH OF CHILDREN

keep out of reach ofchildren.In case of overdose,got medical helpor contact a Poison Control Center right away

INDICATIONS AND USAGE

Apply a suitable amount to the darkened area.

Uses
Uneven skin tone
Spot removal for desired area

When using this product
Swipe onto a clean face, moming and/or evening
Do not rinse.
For daytime use, follow with sunscreen